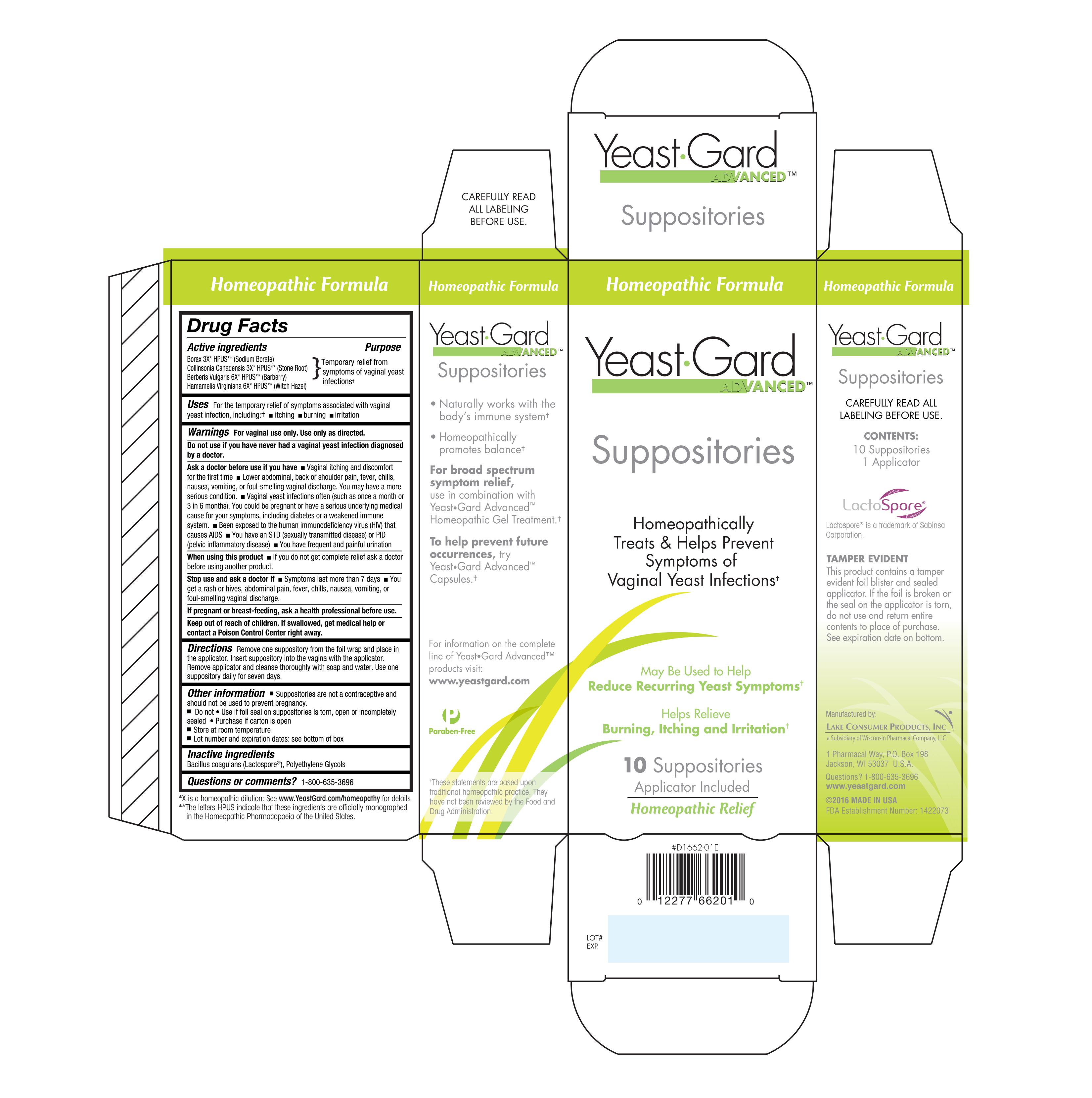 DRUG LABEL: Yeast Gard Advanced
NDC: 68093-7106 | Form: SUPPOSITORY
Manufacturer: Wisconsin Pharmacal Company
Category: homeopathic | Type: HUMAN OTC DRUG LABEL
Date: 20181206

ACTIVE INGREDIENTS: BERBERIS VULGARIS ROOT BARK 6 [hp_X]/1 1; SODIUM BORATE 3 [hp_X]/1 1; COLLINSONIA CANADENSIS ROOT 3 [hp_X]/1 1; HAMAMELIS VIRGINIANA ROOT BARK/STEM BARK 6 [hp_X]/1 1
INACTIVE INGREDIENTS: POLYETHYLENE GLYCOL 400; BACILLUS COAGULANS; POLYETHYLENE GLYCOL 1450

Drug Facts

Active ingredients
Borax 3X HPUS
Collinsonia Canadensis 3x HPUS
Berberis Vulgaris 6X HPUS
Hamamelis Virginiana 6X HPUS

Purpose

Temporary relief from symptoms of vaginal yeast infections

INDICATIONS AND USAGE

Uses For the temporary relief of symptoms associated with vaginal yeast infection, including;

- itching
- burning
- irritation

Warnings

For vaginal use only. Use only as directed.

Do not use if you have never had a vaginal yeast infection diagnosed by a doctor.

Stop use and ask a doctor if:

- Symptoms last more than 7 days
- You get a rash or hives, abdominal pain, fever, chills, nausea, vomiting, or foul-smelling vaginal discharge.

PREGNANCY OR BREAST FEEDING

If pregnant or breast-feeding, ask a health professional before use.

Keep out of reach of children. If swallowed, get medical help or contact a Poison Control Center right away.

Ask a doctor before use if you have

- Vaginal itching and discomfort for the first time
- Lower abdominal, back or shoulder pain, fever, chills, nausea, vomiting, or foul-smelling vaginal discharge. You may have a serious condition.
- Vaginal yeast infections often (such as once a month or 3 in 6 months). You could be pregnant or have a serious underlying medical cause for you symptoms, including diabetes or a weakened immune system.
- Been exposed to the human immunodeficiency virus (HIV) that causes AIDS
- You have an STD (sexually transmitted disease) or PID (Pelvic inflammatory disease)
- You have frequent and painful urination

When using this product

- if you do not get complete relief ask a doctor before using another product,

Directions

Remove one suppository from the foil wrap and place in the applicator. Insert suppository into the vagina with the applicator. Remove applicator and cleanse thoroughly with soap and water. Use one suppository daily for seven days.

Other information

- Suppositories are not a contraceptive and should not be used to prevent pregnancy.
- Do not Use if foil seal on suppositories is torn, open or incompletely sealed, Purchase if carton is open
- Store at room temperature
- Lot number and expiration dates: see bottom of box

Inactive Ingredients

Bacillus coagulans, Polyethylene Glycols

Questions or comments?

1-800-635-3696